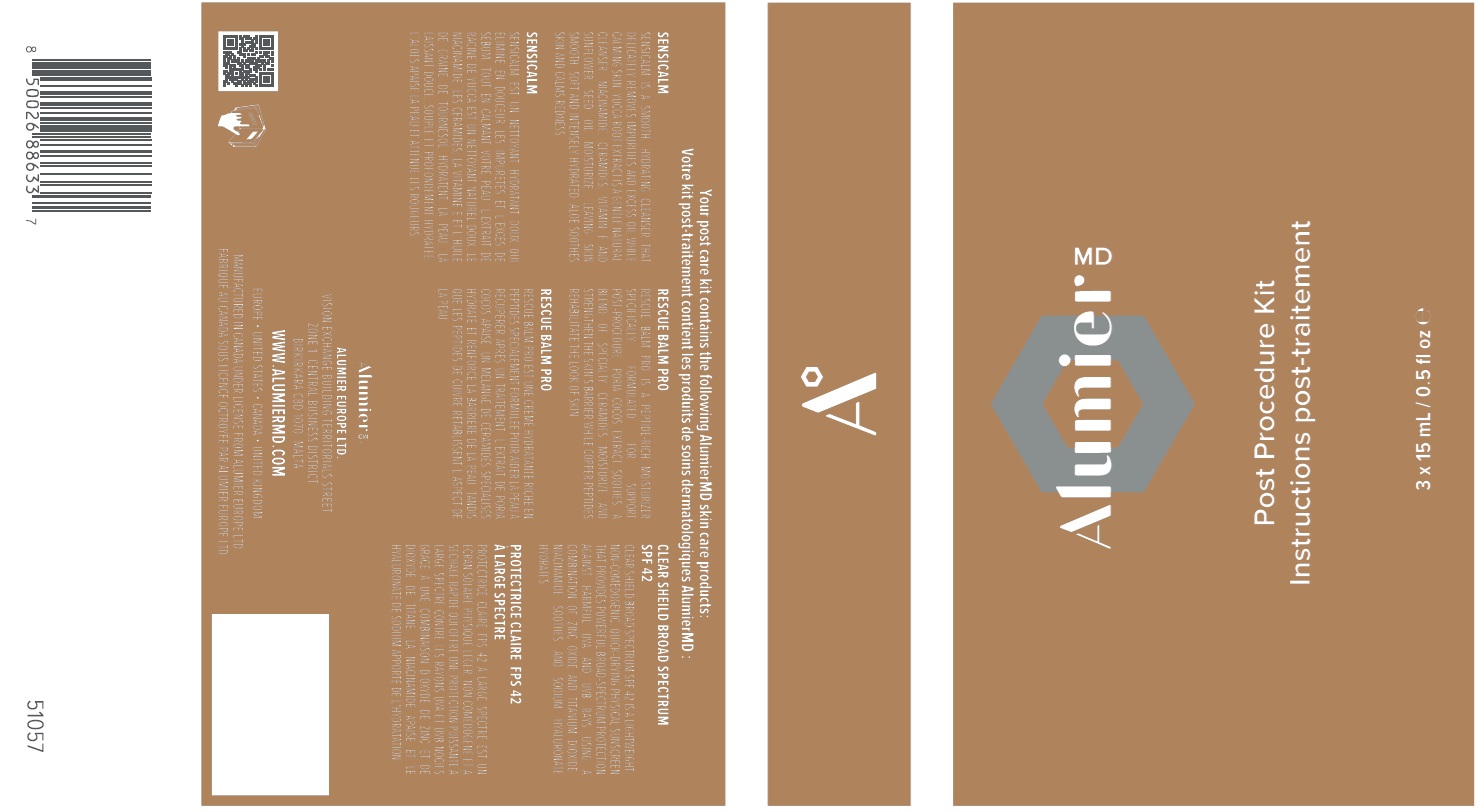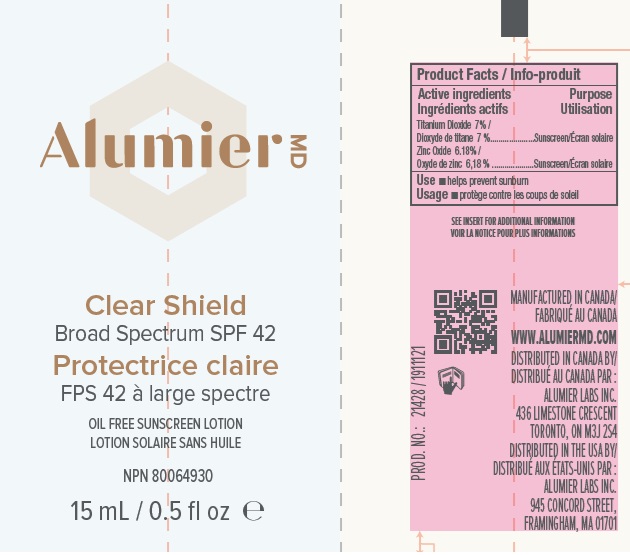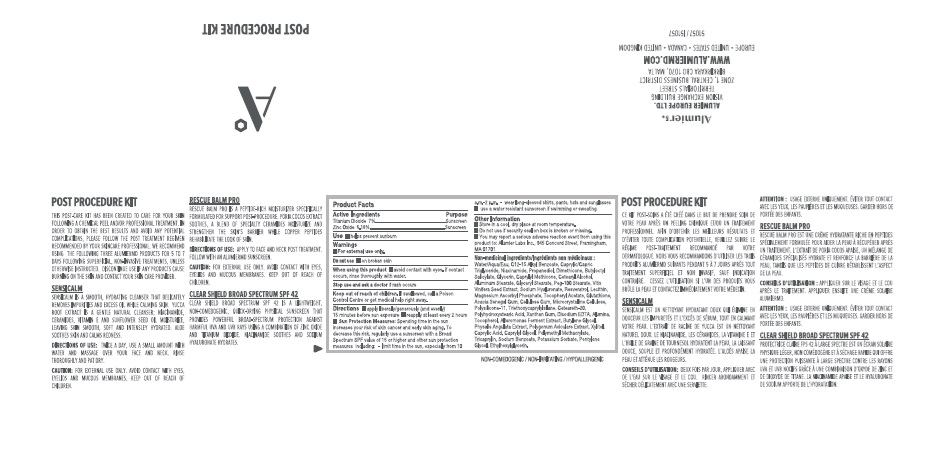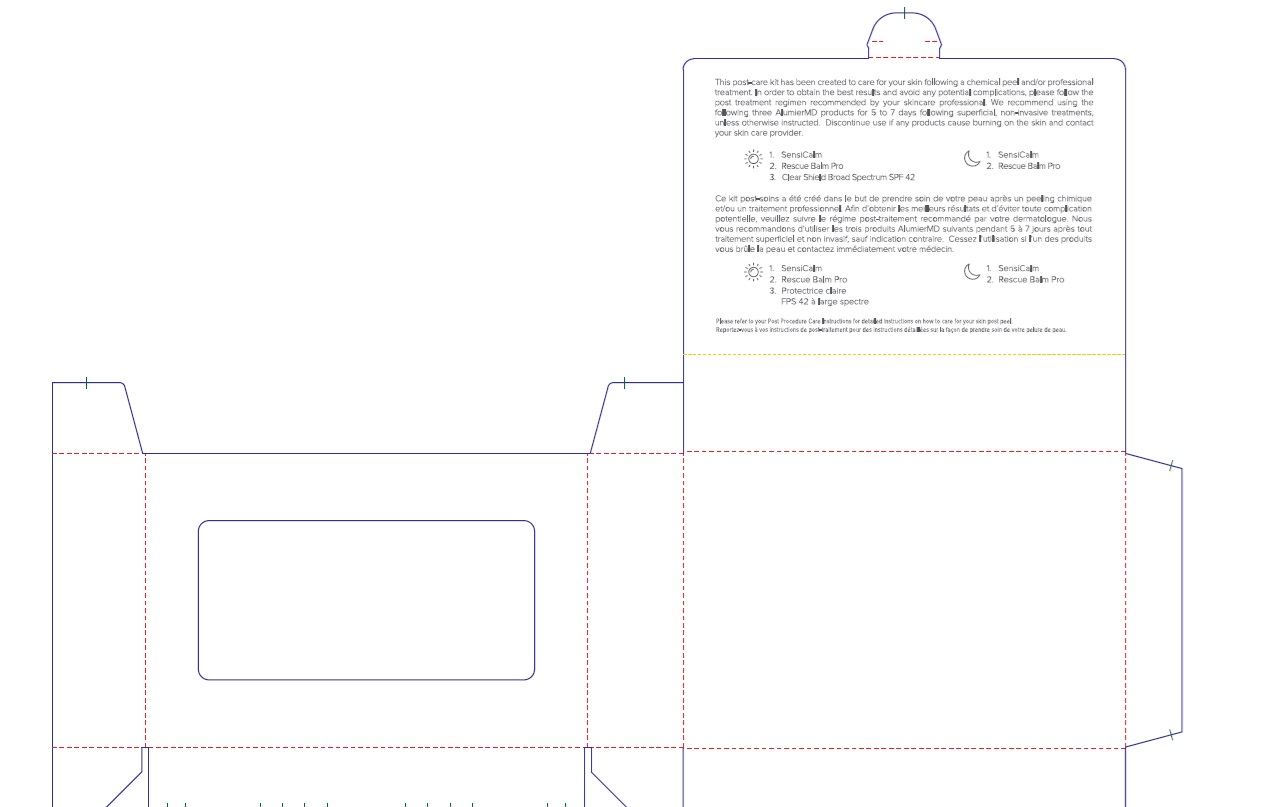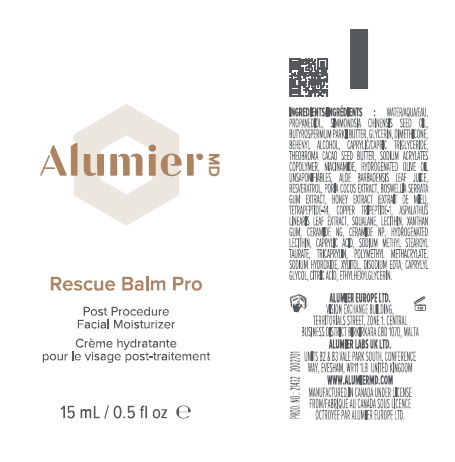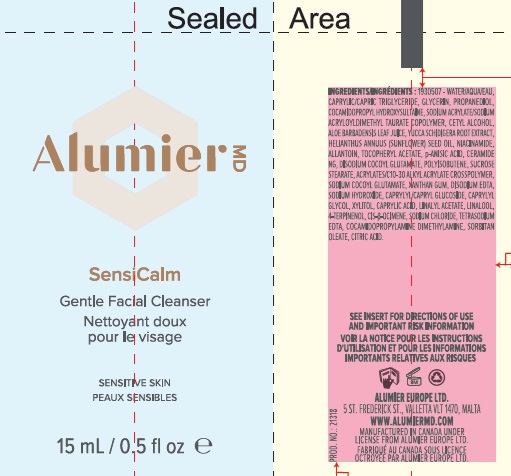 DRUG LABEL: Alumier MD Post Procedure Kit
NDC: 69473-019 | Form: KIT | Route: TOPICAL
Manufacturer: Alumier Labs
Category: otc | Type: HUMAN OTC DRUG LABEL
Date: 20241023

ACTIVE INGREDIENTS: ZINC OXIDE 61.8 mg/1 mL; TITANIUM DIOXIDE 70 mg/1 mL
INACTIVE INGREDIENTS: XYLITOL; CAPRYLIC ACID; ETHYLHEXYLGLYCERIN; HYALURONATE SODIUM; LECITHIN, SUNFLOWER; POLYHYDROXYSTEARIC ACID (2300 MW); BUTYLENE GLYCOL; TRICAPRYLIN; NIACINAMIDE; CAPRYLYL METHICONE; POLYGONUM AVICULARE TOP; TRIETHOXYCAPRYLYLSILANE; WATER; GLYCERYL MONOSTEARATE; ACACIA; POLYOXYL 20 CETOSTEARYL ETHER; MAGNESIUM ASCORBYL PHOSPHATE; BUTYLOCTYL SALICYLATE; GLYCERIN; VITIS VINIFERA SEED; ALUMINUM MONOSTEARATE; MEDIUM-CHAIN TRIGLYCERIDES; XANTHAN GUM; ALKYL (C12-15) BENZOATE; PROPANEDIOL; CARBOXYMETHYLCELLULOSE SODIUM, UNSPECIFIED FORM; .ALPHA.-TOCOPHEROL ACETATE; MICROCRYSTALLINE CELLULOSE; EDETATE DISODIUM; CETOSTEARYL ALCOHOL; PEG-100 STEARATE; ALUMINUM OXIDE; GLUTATHIONE; PHENOXYETHANOL; RESVERATROL; TOCOPHEROL; PHYSALIS ANGULATA; POLY(METHYL METHACRYLATE; 450000 MW); SODIUM BENZOATE; DIMETHICONE; CAPRYLYL GLYCOL; PENTYLENE GLYCOL; POTASSIUM SORBATE; DIMETHICONE/VINYL DIMETHICONE CROSSPOLYMER (SOFT PARTICLE)

Alumier MD Post Procedure Kit

Active Ingredients

Titanium Dioxide 7%

Zinc Oxide 6.18%

Purpose

Sunscreen

Use

- helps prevent sunburn

Warnings

Do not use

- on broken skin

When using this product

- avoid contact with eyes. If contact occurs, rinse thoroughly with water.

Stop use and ask a doctor

if rash occurs

Keep out of reach of children

If swallowed, call a Poison Control Centre or get medical help right away.

Directions

- apply liberally/generously (and evenly) 15 minutes before sun exposure
- reapply at least every 2 hours
- Sun Protection Measures: Spending time in the sun increases your risk of skin cancer and early skin aging. To decrease this risk, regularly use a sunscreen with a Broad Spectrum SPF value of 15 or higher and other sun protection measures including: - limit time in the sun, especially from 10 a.m. - 2 p.m. - wear long-sleeved shirts, pants, hats and sunglasses
- use a water resistant sunscreen if swimming or sweating

Other Information

- Store in a cool, dry place at room temperature.
- Do not use if security seal on box is broken or missing.
- You may report a serious adverse reaction event from using this product to: Alumier Labs Inc., 945 Concord Street, Framingham, MA 01701

Non-medicinal ingredients

Water/Aqua/Eau, C12-15 Alkyl Benzoate, Caprylic/Capric Triglyceride, Niacinamide, Propanediol, Dimethicone, Butyloctyl Salicylate, Glycerin, Caprylyl Methicone, Cetearyl Alcohol, Aluminium Stearate, Glyceryl Stearate, PEG-100 Stearate, Vitis Vinifera Seed Extract, Sodium Hyaluronate, Resveratrol, Lecithin, Magnesium Ascorbyl Phosphate, Tocopheryl Acetate, Glutathione, Acacia Senegal Gum, Cellulose Gum, Microcrystalline Cellulose, Polysilicone-11, Triethoxycaprylylsilane, Ceteareth-20, Polyhydroxystearic Acid, Xanthan Gum, Disodium EDTA, Alumina, Tocopherol, Alteromonas Ferment Extract, Butylene Glycol, Physalis Angulata Extract, Polygonum Aviculare Extract, Xylitol, Caprylic Acid, Caprylyl Glycol, Polymethyl Methacrylate, Tricaprylin, Sodium Benzoate, Potassium Sorbate, Pentylene Glycol, Ethylhexylglycerin.